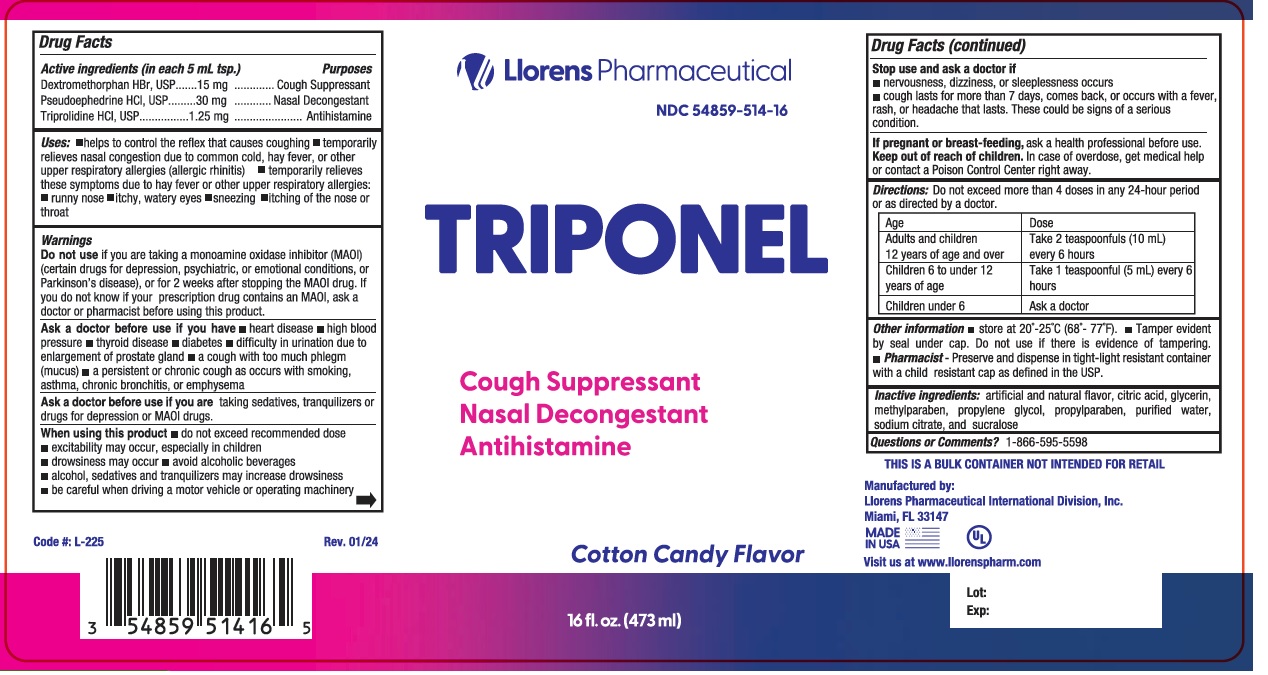 DRUG LABEL: Triponel
NDC: 54859-514 | Form: LIQUID
Manufacturer: Llorens Pharmaceutical International Division, Inc.
Category: otc | Type: HUMAN OTC DRUG LABEL
Date: 20251231

ACTIVE INGREDIENTS: DEXTROMETHORPHAN HYDROBROMIDE 15 mg/5 mL; PSEUDOEPHEDRINE HYDROCHLORIDE 30 mg/5 mL; TRIPROLIDINE HYDROCHLORIDE 30 mg/5 mL
INACTIVE INGREDIENTS: ANHYDROUS CITRIC ACID; GLYCERIN; METHYLPARABEN; PROPYLENE GLYCOL; PROPYLPARABEN; WATER; SODIUM CITRATE; SUCRALOSE

Llorens-Triponel 514

Active Ingredients

Dextromethorphan HBr

Pseudoephedrine HCl

Triprolidine HCl

Purpose

Cough Suppressant

Nasal Decongestant

Antihistamine

Uses

- helps to control the reflex that causes coughing
- temporarily relieves nasal congestion due to common cold, hay fever, or other upper respiratory allergies (allergic: rhinitis)
- temporarily relieves these symptoms due to hay fever or upper respiratory allergies:
- runny nose
- itchy, watery eyes
- sneezing
- itching of the nose or throat

Warnings

Do not use if you are taking a monoamine oxidase inhibitor (MAOI) (certain drugs for drepssion, psychiatric, or emotional conditions, or Parkinson's disease), or for 2 weeks after stopping the MAOI drug. If you do not know if your presciption drug conatins an MAOI, ask a doctor or pharmacist before using this product.

Ask a doctor before use if you have

- heart disaese
- high blood pressure
- thyroid disease
- diabetes
- difficulty in urination due to an enlargment of the prostate gland
- a cough with too much phlegm (mucus)
- a persistent or chronic cough as occurs with smoking, asthma, chronic bronchitis, or emphysema

Ask a doctor before use if you are taking sedatives, transquilizers or drugs for depression or MAOI drugs.

When using this product

- do not exceed recommended dose
- excitability may occur, especially in children
- drowsiness may occur
- avoid alcoholic beverages
- alcohol, sedative and tranquilizers may increase drowsiness
- be careful when driving a motor vehicle or operating machiney

Stop use and ask a doctor if

- nervoisness, dizziness or sleeplessness occurs
- cough lasts for more than 7 days, comes back, or occurs with a fever, rash or headache that lasts. These could be signs of a serious condition.

PREGNANCY OR BREAST FEEDING

If pregnant or breast-feeding, ask a health prodessional before use.

Keep out of reach of children. In case of overdose, get medical help or contact Poinson Control Center right away.

DOSAGE AND ADMINISTRATION

Directions: Do not exceed more than 4 doses in any 24-hour period or as directed by a doctor.

Age | Dose
Adults and children 12 years of age and over | Take 2 teaspoonfuls (10 mL) every 6 hours
Children 6 to under 12 years of age | Take 1 teaspoonful (5mL) every 6 hours
Children under 6 | Ask a doctor

INACTIVE INGREDIENT

Inactive ingredients artificial flavor, citric acid, glycerin, methylparaben, propylene glycol, propylparaben, purified water, sodium citrate, and sucralose.

Questions or Comments? 1-866-595-5598